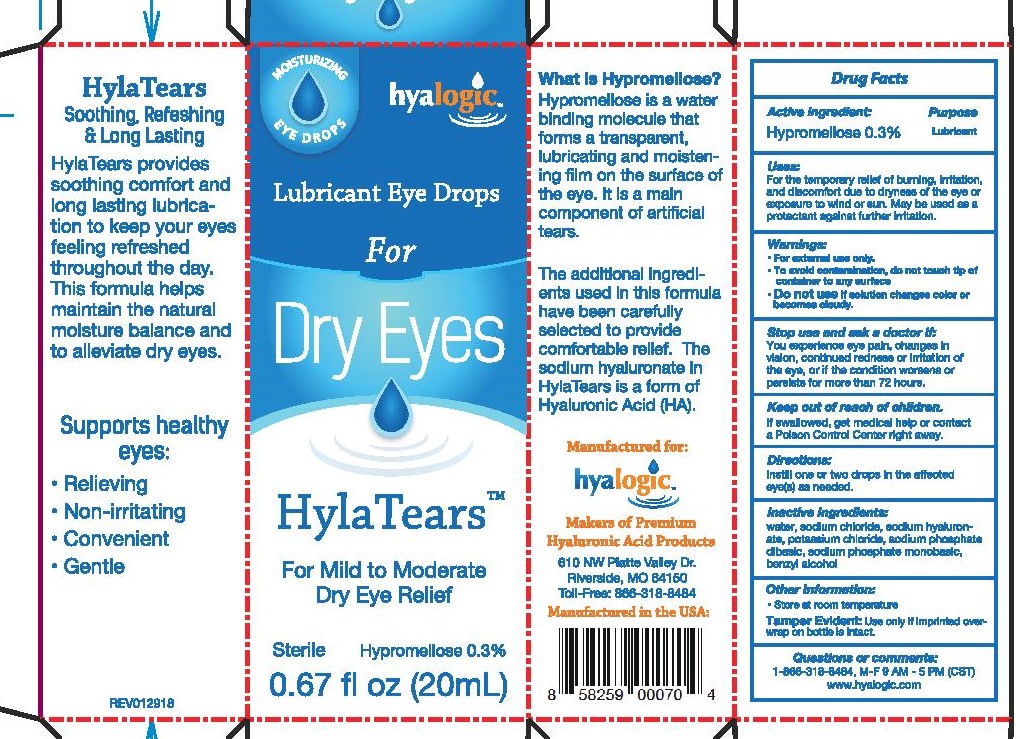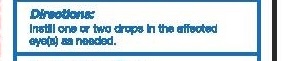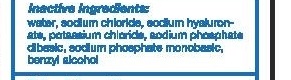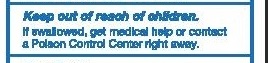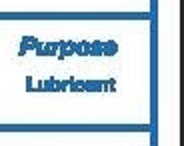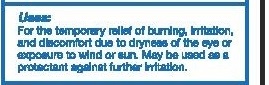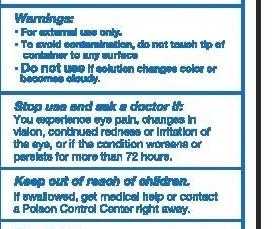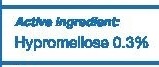 DRUG LABEL: HylaTears
NDC: 72094-001 | Form: LIQUID
Manufacturer: Hyalogic LLC
Category: otc | Type: HUMAN OTC DRUG LABEL
Date: 20220210

ACTIVE INGREDIENTS: HYPROMELLOSE 2910 (4000 MPA.S) 3 mg/10 mL
INACTIVE INGREDIENTS: WATER; SODIUM CHLORIDE; HYALURONATE SODIUM; POTASSIUM CHLORIDE; SODIUM PHOSPHATE DIBASIC DIHYDRATE; SODIUM PHOSPHATE, MONOBASIC, UNSPECIFIED FORM; BENZYL ALCOHOL

Hyalogic Hyla Tears-corrected one of the inactive ingredients-added updated box under principle display panel.